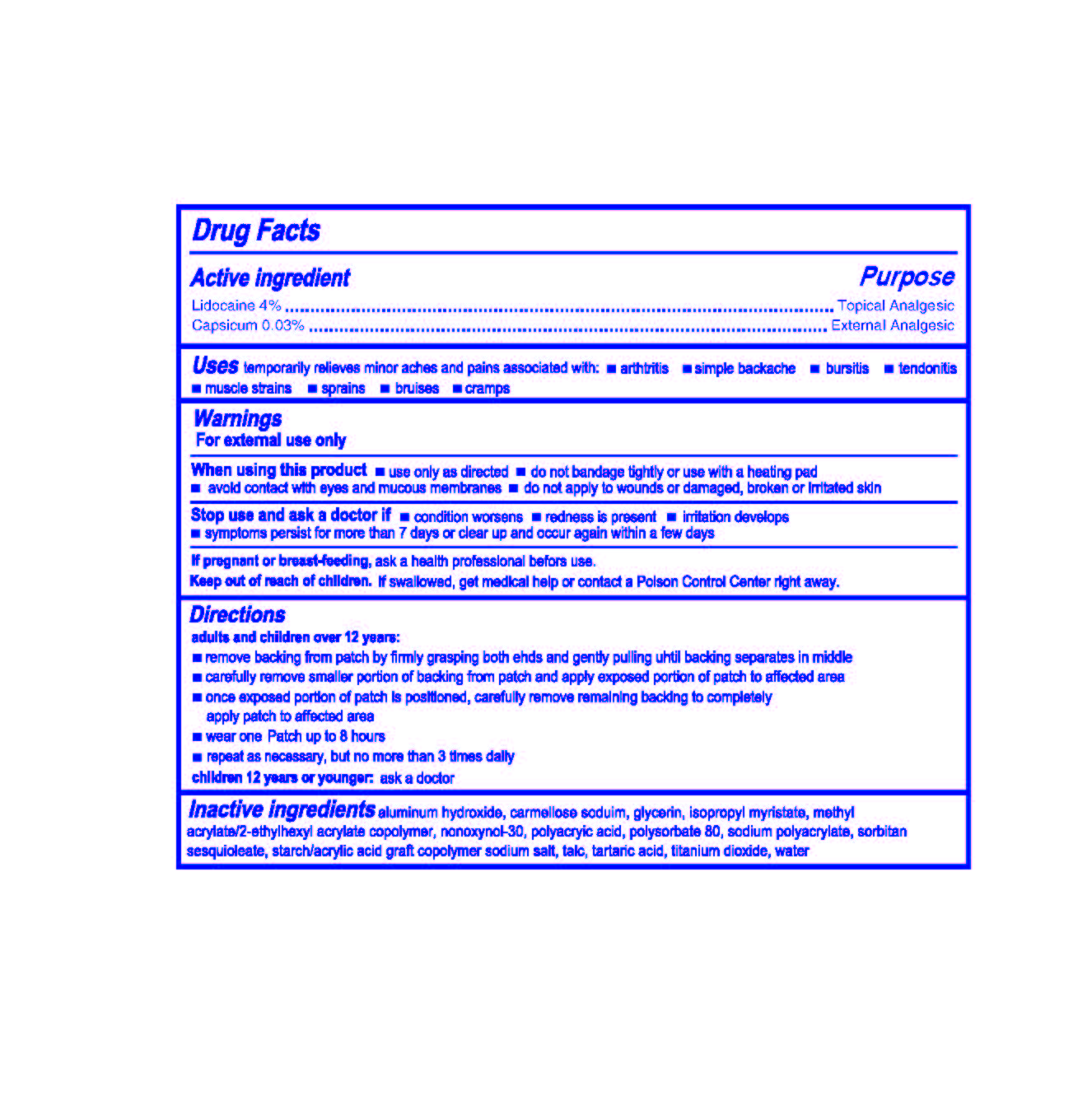 DRUG LABEL: Odynia-U
                
NDC: 69647-003 | Form: PATCH
Manufacturer: Ursh Pharmaceutical Inc.
Category: otc | Type: HUMAN OTC DRUG LABEL
Date: 20150514

ACTIVE INGREDIENTS: LIDOCAINE 4 g/100 g; CAPSICUM .03 g/100 g
INACTIVE INGREDIENTS: ALUMINUM HYDROXIDE; CARBOXYMETHYLCELLULOSE SODIUM, UNSPECIFIED FORM; GLYCERIN; ISOPROPYL MYRISTATE; METHYL ACRYLATE; 2-ETHYLHEXYL ACRYLATE; NONOXYNOL-30; POLYACRYLIC ACID (250000 MW); POLYSORBATE 80; SODIUM POLYACRYLATE (2500000 MW); SORBITAN SESQUIOLEATE; ACRYLIC ACID; SODIUM; SODIUM CHLORIDE; TALC; TARTARIC ACID; TITANIUM DIOXIDE; WATER

Drug Facts

Active Ingredient

Lidocaine 4 %

Capsicum 0.03 %

Purpose

Topical Analgesic

External Analgesic

INDICATIONS AND USAGE

Uses temporarily relieves minor aches and pains associated with: -arthritis -simple backache --bursitis --tendonitis

--muscle strains --sprains --bruises --cramps

Warnings

For external use only

When using this product -use only as directed -do not bandage tightly or use with a heating pad

-avoid contact with eyes and mucus membranes -do not apply to wounds or damaged, broken or irritated skin

Stop use and ask a doctor if -condition worsens -redness is present -irritation develops

-symptoms persist for more than 7 days or clear up and occur again within a few days

PREGNANCY OR BREAST FEEDING

If pregnant or breast feeding, ask a health professional before use

Keep out of reach of children. If swallowed, get medical help or contact a Poison Control Center right away

Directions

adults and children over 12 years:

-remove backing from patch by firmly grasping both ends and gently pulling until backing separates in middle

-carefully remove smaller portion of backing from patch and apply exposed portion of patch to affected area

-once exposed portion of patch is positioned, carefully remove remaining backing to completely

apply patch to affected area

-wear one Icy Hot Patch up to 8 hours

-repeat as necessary, but no more than 3 times daily

children under 12 years or younger: ask a doctor

INACTIVE INGREDIENT

Inactive ingredients aluminum hydroxide, carmellose sodium, glycerin, isopropyl myristate, methyl

acrylate / 2 -ethylhexyl acrylate copolymer, nonoxynol-30, polyacryic acid, polysorbate 80, sodium polyacrylate, sorbitan

sesquioleate, starch / acrylic acid graft copolymer sodium salt, talc, tartaric acid, titanium dioxide, water